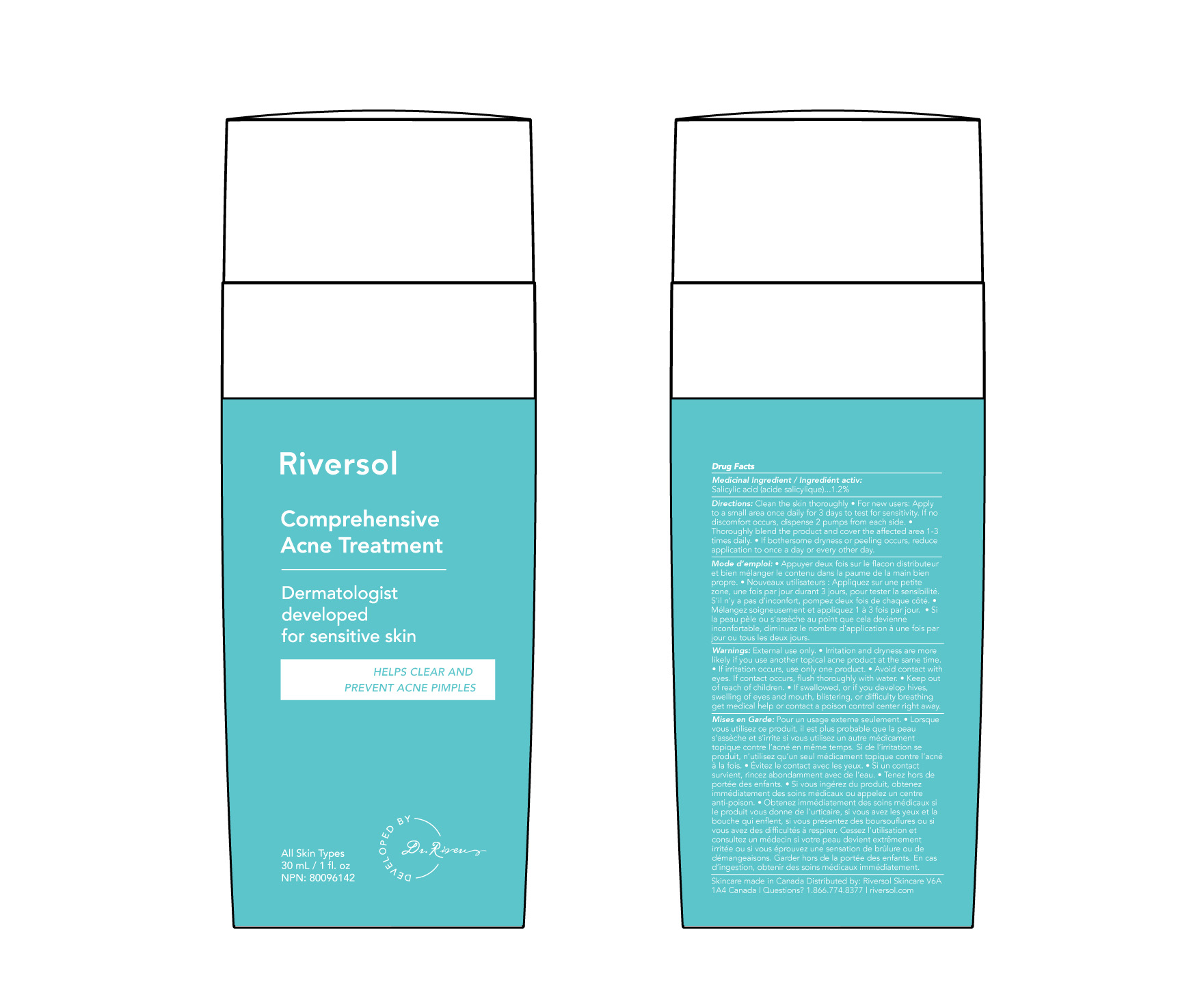 DRUG LABEL: Riversol Comprehensive Acne Treatment
NDC: 72019-0002 | Form: LOTION
Manufacturer: Riversol Skincare Solutions Inc
Category: otc | Type: HUMAN OTC DRUG LABEL
Date: 20220331

ACTIVE INGREDIENTS: SALICYLIC ACID 0.18 g/30 g
INACTIVE INGREDIENTS: CITRIC ACID MONOHYDRATE; MEDIUM-CHAIN TRIGLYCERIDES; WATER; POLYSORBATE 60; OCTYLDODECANOL; 1,9-DECADIENE; XANTHAN GUM; PROPYLENE GLYCOL; PHENOXYETHANOL; SODIUM HYDROXIDE; SODIUM NITRITE; GLYCERYL MONOSTEARATE; CETOSTEARYL ALCOHOL; PEG-100 STEARATE

Medicinal Ingredient / Ingrédient médicinal:

Salicylic acid (acide salicylique).... 1.2%

Directions:

Clean the skin thoroughly • For new users: Apply to a small area once daily for 3 days to test for sensitivity. If no discomfort occurs, dispense 2 pumps from each side. • Thoroughly blend the product and cover the affected area 1-3 times daily. • If bothersome dryness or peeling occurs, reduce application to once a day or every other day.

Warnings:

External use only. • Irritation and dryness are more likely if you use another topical acne product at the same time. If irritation occurs, use only one product. • Avoid contact with eyes. If contact occurs, flush thoroughly with water. • Keep out of reach of children. • If swallowed, or if you develop hives, swelling of eyes or mouth, blistering, or difficulty breathing get medical help or contact a poison control center right away.

DOSAGE AND ADMINISTRATION

Directions: Clean the skin thoroughly • For new users: Apply to a small area once daily for 3 days to test for sensitivity. If no discomfort occurs, dispense 2 pumps from each side. • Thoroughly blend the product and cover the affected area 1-3 times daily. • If bothersome dryness or peeling occurs, reduce application to once a day or every other day.

Non-Medical Ingredients

Ingrédients non médicinaux:
Aqua, Octyldodecanol,
Caprylic/capric triglyceride,
Cetearyl alcohol/Sodium lauryl
sulfate/Sodium cetearyl sulfate,
Polysorbate 60, PVM/MA
Decadiene Crosspolymer,
Acrylates/C10-30 Alkyl Acrylate
Crosspolymer, Xanthan Gum,
Propylene glycol,
Phenoxyethanol, Sodium
hydroxide, Citric acid, Sodium
nitrite, Glyceryl Stearate,
PEG-100

Warnings

• Keep out of reach
of children. •

PURPOSE

For the management of acne

Warnings

External use only. • Irritation and dryness
are more likely if you use another topical
acne product at the same time. • If irritation
occurs, use only one product. • Avoid
contact with eyes. If contact occurs, flush
thoroughly with water. • Keep out of reach
of children. • If swallowed, or if you develop
hives, swelling of eyes and mouth,
blistering, or difficulty breathing get medical
help or contact a poison control center right
away.

Directions

For new users: Apply to a small area once daily for 3 days to test for sensitivity. If no discomfort occurs, dispense 2 pumps from each side. • Thoroughly blend the product and cover the affected area 1-3 times daily. • If bothersome dryness or peeling occurs, reduce application to once a day or every other day.

RECENT MAJOR CHANGES

Section changed: Dosage & administration section. Incorporated 07/2021

Previous text: If no discomfort occurs, thoroughly mix two pumps into the palm of a clean hand and cover affected area 1-3 times daily.

Updated text: If no discomfort occurs, dispense 2 pumps from each side.

PACKAGE LABEL

FRONT:

Comprehensive Acne Treatment Dermatologist developed for sensitive skin Helps clear and prevent acne pimples All skin types 30ml / 1 fl oz Developed by Dr. Rivers

Back:

Drug Facts
Medicinal Ingredient / Ingrediént activ:
Salicylic acid (acide salicylique)...1.2%

Directions: Clean the skin thoroughly • For new users: Apply to a small area once daily for 3 days to test for sensitivity. If no discomfort occurs, dispense 2 pumps from each side. • Thoroughly blend the product and cover the affected area 1-3 times daily. • If bothersome dryness or peeling occurs, reduce application to once a day or every other day.

Mode d’emploi: • Appuyer deux fois sur le flacon distributeur et bien mélanger le contenu dans la paume de la main bien propre. • Nouveaux utilisateurs : Appliquez sur une petite zone, une fois par jour durant 3 jours, pour tester la sensibilité. S’il n’y a pas d’inconfort, pompez deux fois de chaque côté. • Mélangez soigneusement et appliquez 1 à 3 fois par jour. • Si la peau pèle ou s’assèche au point que cela devienne inconfortable, diminuez le nombre d'application à une fois par jour ou tous les deux jours.

Warnings: External use only. • Irritation and dryness are more likely if you use another topical acne product at the same time. • If irritation occurs, use only one product. • Avoid contact with eyes. If contact occurs, flush thoroughly with water. • Keep out of reach of children. • If swallowed, or if you develop hives, swelling of eyes and mouth, blistering, or difficulty breathing get medical help or contact a poison control center right away.

Mises en Garde: Pour un usage externe seulement. • Lorsque vous utilisez ce produit, il est plus probable que la peau s’assèche et s’irrite si vous utilisez un autre médicament topique contre l’acné en même temps. Si de l’irritation se produit, n’utilisez qu’un seul médicament topique contre l’acné à la fois. • Évitez le contact avec les yeux. • Si un contact survient, rincez abondamment avec de l’eau. • Tenez hors de portée des enfants. • Si vous ingérez du produit, obtenez immédiatement des soins médicaux ou appelez un centre anti-poison. • Obtenez immédiatement des soins médicaux si le produit vous donne de l’urticaire, si vous avez les yeux et la bouche qui enflent, si vous présentez des boursouflures ou si vous avez des difficultés à respirer. Cessez l’utilisation et consultez un médecin si votre peau devient extrêmement irritée ou si vous éprouvez une sensation de brûlure ou de démangeaisons. Garder hors de la portée des enfants. En cas d’ingestion, obtenir des soins médicaux immédiatement.

Skincare made in Canada Distributed by: Riversol Skincare V6A 1A4 Canada | Questions? 1.866.774.8377 | riversol.com